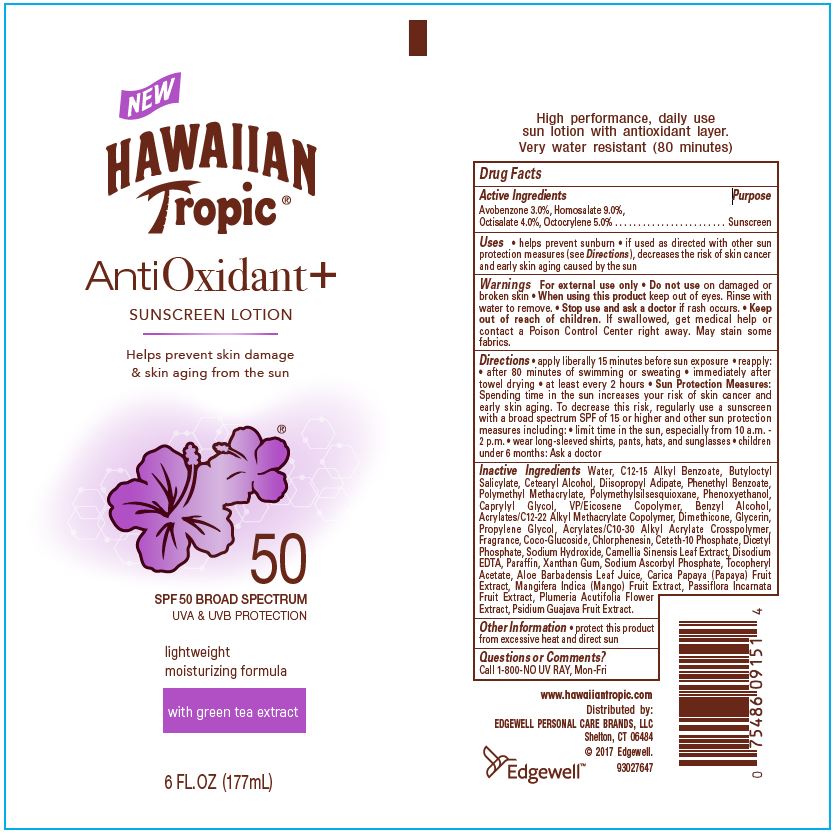 DRUG LABEL: Hawaiian Tropic
NDC: 63354-929 | Form: LOTION
Manufacturer: Edgewell Personal Care Brands LLC
Category: otc | Type: HUMAN OTC DRUG LABEL
Date: 20241031

ACTIVE INGREDIENTS: AVOBENZONE 3 g/100 g; OCTISALATE 4 g/100 g; HOMOSALATE 9 g/100 g; OCTOCRYLENE 5 g/100 g
INACTIVE INGREDIENTS: COCO GLUCOSIDE; CETOSTEARYL ALCOHOL; DIMETHICONE; DIHEXADECYL PHOSPHATE; .ALPHA.-TOCOPHEROL ACETATE; ALOE VERA LEAF; PLUMERIA RUBRA FLOWER; MANGO; CARICA PAPAYA WHOLE; ALKYL (C12-15) BENZOATE; PHENETHYL BENZOATE; CAPRYLYL GLYCOL; GLYCERIN; BENZYL ALCOHOL; CETETH-10 PHOSPHATE; SODIUM ASCORBYL PHOSPHATE; PARAFFIN; CHLORPHENESIN; SODIUM HYDROXIDE; CAMELLIA SINENSIS WHOLE; XANTHAN GUM; PSIDIUM GUAJAVA WHOLE; PASSIFLORA INCARNATA FRUIT; WATER; BUTYLOCTYL SALICYLATE; POLYMETHYLSILSESQUIOXANE (11 MICRONS); DIISOPROPYL ADIPATE; VINYLPYRROLIDONE/EICOSENE COPOLYMER; PROPYLENE GLYCOL; EDETATE DISODIUM; POLY(METHYL METHACRYLATE; 450000 MW); CARBOMER INTERPOLYMER TYPE A (ALLYL SUCROSE CROSSLINKED); PHENOXYETHANOL

Active Ingredients

Avobenzone 3%, Homosalate 9%, Octisalate 4%, Octocrylene 5%

Purpose

Sunscreen

Uses

Helps prevent sunburn

If used as directed with other sun protection measures (see Directions), decreases the risk of skin cancer and early skin aging caused by the sun.

Warnings

For external use only

Do not use

on damaged or broken skin

When using this product

keep out of eyes. Rinse with water to remove

Stop use and ask a doctor

if rash occurs

Keep out of reach of children

If swallowed, get medical help or contact a Poison Control Center right away. May stain some fabrics.

Directions

•Apply liberally 15 minutes before sun exposure • Reapply: • after 80 minutes of swimming or sweating • immediately after towel drying •at least every 2 hours.

Sun Protection Measures: •Spending time in the sun increases your risk of skin cancer and early skin aging. To decrease this risk, regularly use a sunscreen with a broad spectrum SPF value of 15 or higher and other sun protection measures including: limit time in the sun, especially from 10 a.m. - 2 p.m., wear long-sleeved shirts, pants, hats, and sunglasses. Children under 6 months: Ask a doctor.

Inactive Ingredient

Water, C12-15 Alkyl Benzoate, Butyloctyl Salicylate, Cetearyl Alcohol, Diisopropyl Adipate, Phenethyl Benzoate, Polymethyl Methacrylate, Polymethylsilsesquioxane, Phenoxyethanol, Caprylyl Glycol, VP/Eicosene Copolymer, Benzyl Alcohol, Acrylates/C12-22 Alkyl Methacrylate Copolymer, Dimethicone, Glycerin, Propylene Glycol, Acrylates/C10-30 Alkyl Acrylate Crosspolymer, Fragrance, Coco-Glucoside, Chlorphenesin, Ceteth-10 Phosphate, Dicetyl Phosphate, Sodium Hydroxide, Camellia Sinensis Leaf Extract, Disodium EDTA, Paraffin, Xanthan Gum, Sodium Ascorbyl Phosphate, Tocopheryl Acetate, Aloe Barbadensis Leaf Juice, Carica Papaya (Papaya) Fruit Extract, Mangifera Indica (Mango) Fruit Extract, Passiflora Incarnata Fruit Extract, Plumeria Acutifolia Flower Extract, Psidium Guajava Fruit Extract.

Other Information

Protect this product from excessive heat and direct sun

Questions or Comments?

Call 1-800-NO UV RAY, Mon-Fri

PACKAGE LABEL

HAWAIIAN

Tropic(R)

AntiOxidant+

SUNSCREEN LOTION

Helps prevent skin damage

& skin aging from the sun

50

SPF 50 BROAD SPECTRUM

UVA & UVB PROTECTION

lightweight

moisturing formula

with green tea extract

6 FL. OZ (177 mL)